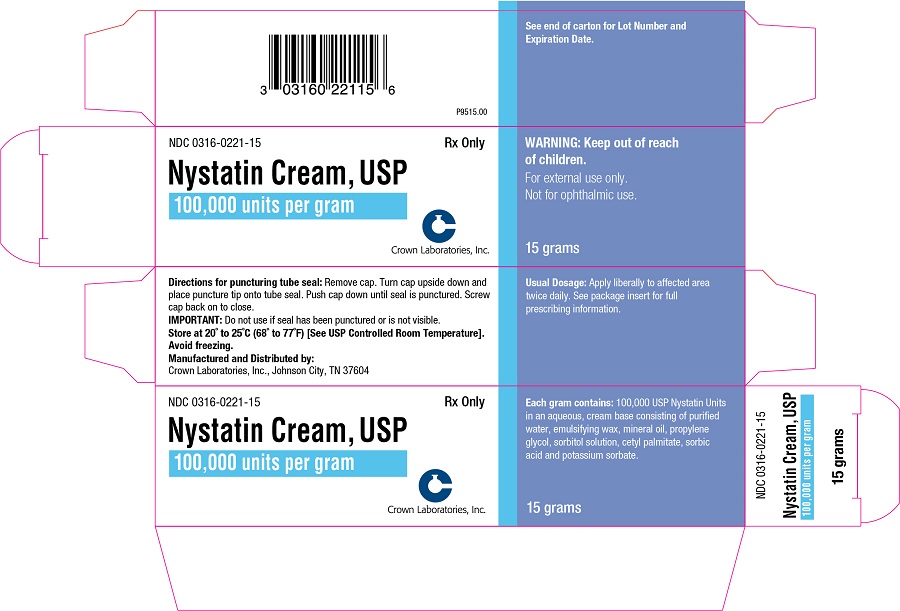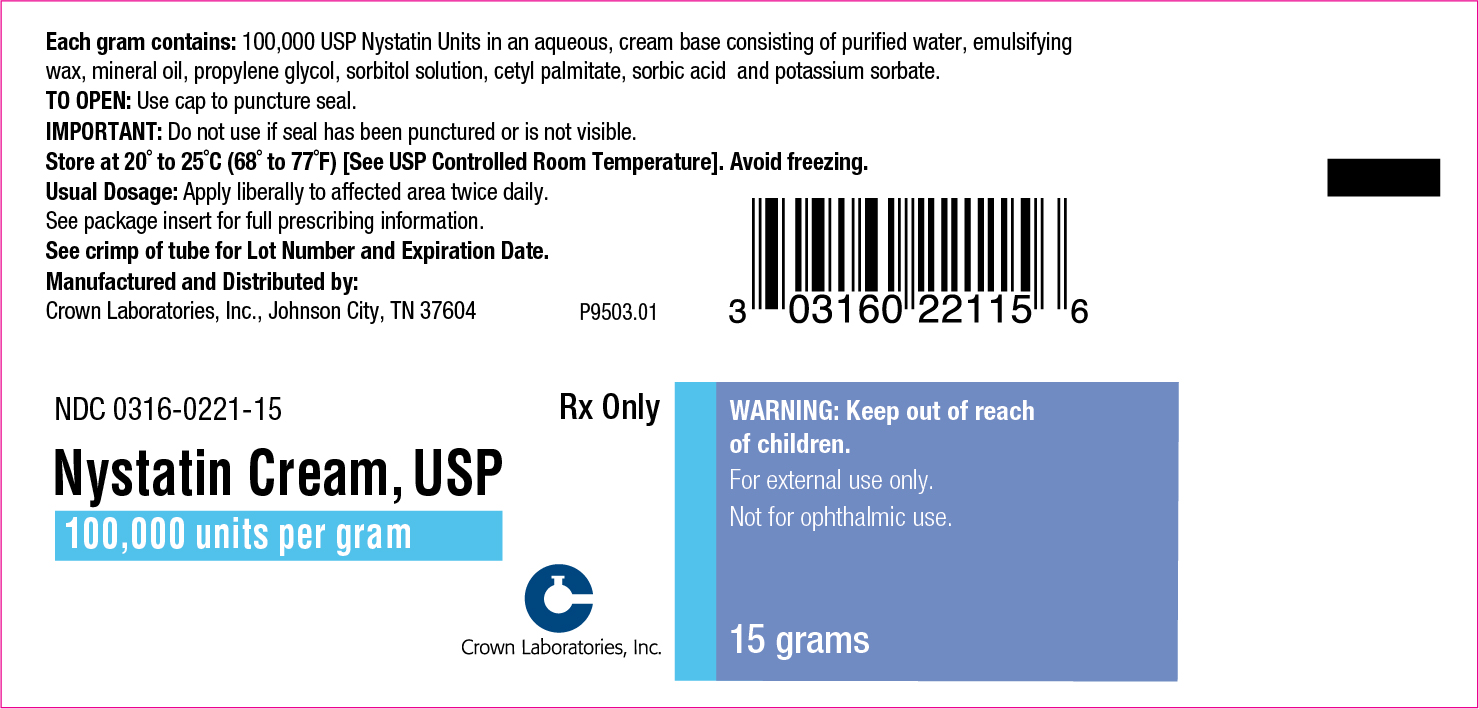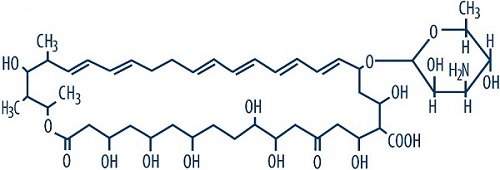 DRUG LABEL: Nystatin Cream
NDC: 0316-0221 | Form: CREAM
Manufacturer: Crown Laboratories
Category: prescription | Type: HUMAN PRESCRIPTION DRUG LABEL
Date: 20260112

ACTIVE INGREDIENTS: NYSTATIN 100000 [USP'U]/1 g
INACTIVE INGREDIENTS: MINERAL OIL; SORBIC ACID; PROPYLENE GLYCOL; WATER; SORBITOL; CETYL PALMITATE; POTASSIUM SORBATE

Nystatin Cream USP

Rx Only

Nystatin Cream, USP

For external use only.

Not for ophthalmic use. Rx Only

DESCRIPTION

Nystatin is a polyene antifungal antibiotic obtained from Streptomyces nursei.

Structural formula:

C47H75NO17 Molecular Weight: 926.13

Nystatin cream is for dermatologic use.

Each gram contains 100,000 USP Nystatin Units in an aqueous, cream base consisting of purified water, emulsifying wax, mineral oil, propylene glycol, sorbitol solution, cetyl palmitate, sorbic acid and potassium sorbate.

CLINICAL PHARMACOLOGY

Pharmacokinetics

Nystatin is not absorbed from intact skin or mucous membrane.

Microbiology

Nystatin is an antibiotic which is both fungistatic and fungicidal in vitro against a wide variety of yeasts and yeast-like fungi, including Candida albicans, C. parapsilosis, C. tropicalis, C. guilliermondi, C. pseudotropicalis, C. krusei, Torulopsis glabrata, Tricophyton rubrum, T. mentagrophytes. Nystatin acts by binding to sterols in the cell membrane of susceptible species resulting in a change in membrane permeability and the subsequent leakage of intracellular components. On repeated subculturing with increasing levels of nystatin, Candida albicans does not develop resistance to nystatin. Generally, resistance to nystatin does not develop during therapy. However, other species of Candida (C. tropicalis, C. guilliermondi, C. krusei, and C. stellatoides) become quite resistant on treatment with nystatin and simultaneously become cross resistant to amphotericin as well. This resistance is lost when the antibiotic is removed. Nystatin exhibits no appreciable activity against bacteria, protozoa, or viruses.

INDICATIONS AND USAGE

Nystatin cream is indicated in the treatment of cutaneous or mucocutaneous mycotic infections caused by Candida albicans and other susceptible Candida species. This cream is not indicated for systemic, oral, intravaginal or ophthalmic use.

CONTRAINDICATIONS

Nystatin cream is contraindicated in patients with a history of hypersensitivity to any of its components.

PRECAUTIONS

General
Nystatin cream should not be used for the treatment of systemic, oral, intravaginal or ophthalmic infections.

If irritation or sensitization develops, treatment should be discontinued and appropriate measures taken as indicated. It is recommended that KOH smears, cultures, or other diagnostic methods be used to confirm the diagnosis of cutaneous or mucocutaneous candidiasis and to rule out infection caused by other pathogens.

INFORMATION FOR THE PATIENT

Patients using this medication should receive the following information and instructions:
1. The patient should be instructed to use this medication as directed (including the replacement of missed doses). This medication is not for any disorder other than that for which it is prescribed.
2. Even if symptomatic relief occurs within the first few days of treatment, the patient should be advised not to interrupt or discontinue therapy until the prescribed course of treatment is completed.
3. If symptoms of irritation develop, the patient should be advised to notify the physician promptly.

Laboratory Tests

If there is a lack of therapeutic response, KOH smears, cultures, or other diagnostic methods should be repeated.

Carcinogenesis, Mutagenesis, Impairment of Fertility

No long-term animal studies have been performed to evaluate the carcinogenic potential of nystatin. No studies have been performed to determine the mutagenicity of nystatin or the effects on male or female fertility.

Pregnancy

Teratogenic Effects
Category C
Animal reproduction studies have not been conducted with any nystatin cream. It also is not known whether this cream can cause fetal harm when used by a pregnant woman or can affect reproductive capacity. Nystatin cream should be prescribed for a pregnant woman only if the potential benefit to the mother outweighs the potential risk to the fetus.

Nursing Mothers

It is not known whether nystatin is excreted in human milk. Caution should be exercised when nystatin is prescribed for a nursing woman.

Pediatric Use

Safety and effectiveness have been established in the pediatric population from birth to 16 years. (See DOSAGE AND ADMINISTRATION.)

Geriatric Use

Clinical studies with nystatin cream did not include sufficient numbers of subjects aged 65 years and older to determine whether they respond differently than younger subjects. Other reported clinical experience has not identified differences in responses between elderly and younger patients, but greater sensitivity of some older individuals cannot be ruled out.

ADVERSE REACTIONS

The frequency of adverse events reported in patients using nystatin cream is less than 0.1%. The more common events that were reported include allergic reactions, burning, itching, rash, eczema, and pain on application. (See PRECAUTIONS: General.)

To report SUSPECTED ADVERSE REACTIONS, contact Crown Laboratories, Inc. at 1-423-926-4413 or FDA at 1-800-FDA-1088 or https://www.fda.gov/Safety/MedWatch/

DOSAGE AND ADMINISTRATION

Adults and Pediatric Patients (Neonates and Older)
Apply liberally to affected areas twice daily or as indicated until healing is complete.

HOW SUPPLIED

Nystatin Cream USP is a light yellow to yellow cream that is supplied in:
15 gram tube NDC 0316-0221-15
30 gram tube NDC 0316-0221-30

Store at 20° to 25°C (68° to 77°F) [see USP Controlled Room Temperature]. Avoid freezing.

Manufactured and Distributed by:
Crown Laboratories, Inc., Johnson City, TN 37604

Printed in USA

P9526.00

15 gram tube

NDC 0316-0221-15

Rx Only

Nystatin Cream, USP

100,000 units per gram

WARNING: Keep out of reach of children.

For external use only.

Not for ophthalmic use.

15 grams

Each gram contains: 100,000 USP Nystatin Units in an aqueous, cream base consisting of purified water, emulsifying wax, mineral oil, propylene glycol, sorbitol solution, cetyl palmitate, sorbic acid and potassium sorbate.

TO OPEN: Use cap to puncture seal.

IMPORTANT: Do not use if seal has been punctured or is not visible.

Store at 20° to 25°C (68° to 77°F) [See USP Controlled Room Temperature]. Avoid freezing.

Usual Dosage: Apply liberally to affected area twice daily. See package insert for full prescribing information.

See crimp of tube for Lot Number and Expiration Date.

Manufactured and Distributed by:

Crown Laboratories, Inc., Johnson City, TN 37604

P9503.01

15 gram carton

NDC 0316-0221-15

Rx Only

Nystatin Cream, USP

100,000 units per gram

WARNING: Keep out of reach of children.

For external use only.

Not for ophthalmic use.

15 grams

Each gram contains: 100,000 USP Nystatin Units in an aqueous, cream base consisting of purified water, emulsifying wax, mineral oil, propylene glycol, sorbitol solution, cetyl palmitate, sorbic acid and potassium sorbate.

Directions for puncturing tube seal: Remove cap. Turn cap upside down and place puncture tip onto tube seal. Push cap down until seal is punctured. Screw cap back on to close.

IMPORTANT: Do not use if seal has been punctured or is not visible.

Store at 20° to 25°C (68° to 77°F) [See USP Controlled Room Temperature]. Avoid freezing.

Usual Dosage: Apply liberally to affected area twice daily. See package insert for full prescribing information.

See end of carton for Lot Number and Expiration Date.

Manufactured and Distributed by:

Crown Laboratories, Inc., Johnson City, TN 37604

P9515.00